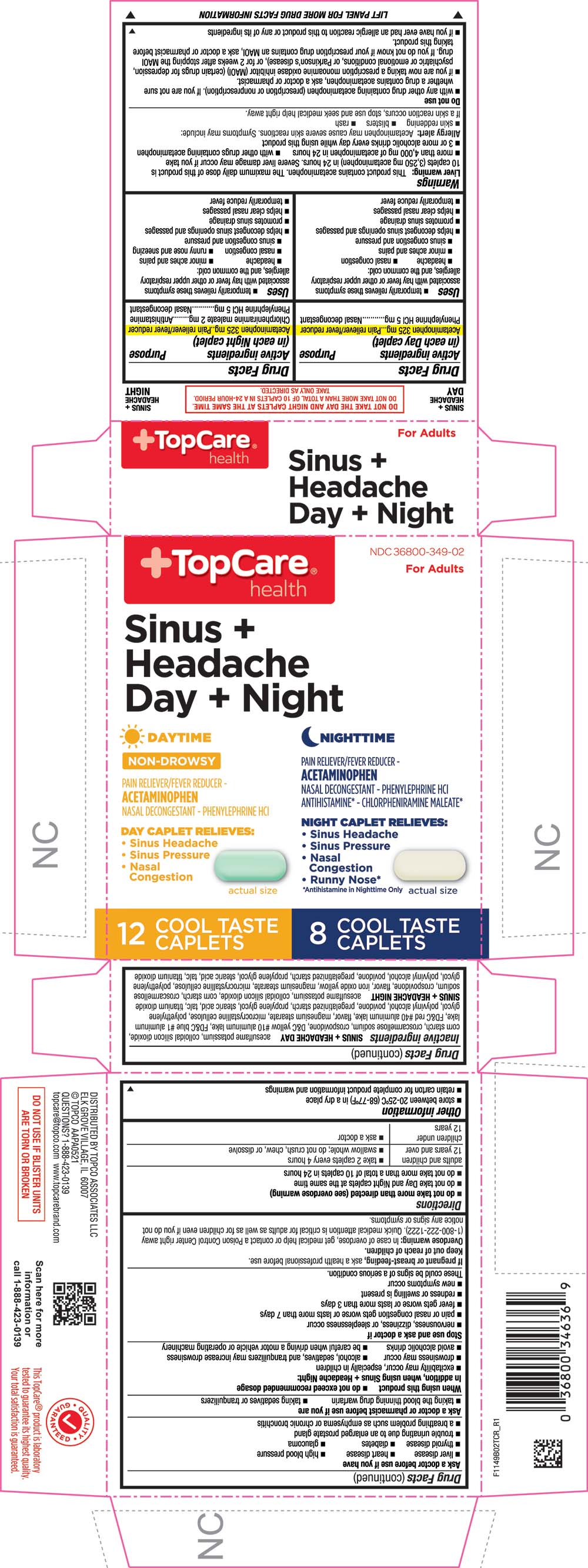 DRUG LABEL: Sinus plus Headache Day and Night
NDC: 36800-349 | Form: KIT | Route: ORAL
Manufacturer: TOPCO ASSOCIATES LLC
Category: otc | Type: HUMAN OTC DRUG LABEL
Date: 20211115

ACTIVE INGREDIENTS: ACETAMINOPHEN 325 mg/1 1; PHENYLEPHRINE HYDROCHLORIDE 5 mg/1 1; ACETAMINOPHEN 325 mg/1 1; CHLORPHENIRAMINE MALEATE 2 mg/1 1; PHENYLEPHRINE HYDROCHLORIDE 5 mg/1 1
INACTIVE INGREDIENTS: ACESULFAME POTASSIUM; SILICON DIOXIDE; CROSCARMELLOSE SODIUM; D&C YELLOW NO. 10; FD&C BLUE NO. 1; FD&C RED NO. 40; ALUMINUM OXIDE; MAGNESIUM STEARATE; CELLULOSE, MICROCRYSTALLINE; POLYETHYLENE GLYCOL, UNSPECIFIED; POLYVINYL ALCOHOL, UNSPECIFIED; POVIDONE, UNSPECIFIED; STARCH, CORN; PROPYLENE GLYCOL; STEARIC ACID; TALC; TITANIUM DIOXIDE; STARCH, CORN; CROSPOVIDONE; PROPYLENE GLYCOL; STEARIC ACID; TALC; TITANIUM DIOXIDE; ACESULFAME POTASSIUM; SILICON DIOXIDE; CROSCARMELLOSE SODIUM; FERRIC OXIDE YELLOW; MAGNESIUM STEARATE; CELLULOSE, MICROCRYSTALLINE; POLYETHYLENE GLYCOL, UNSPECIFIED; POLYVINYL ALCOHOL, UNSPECIFIED; POVIDONE, UNSPECIFIED

1149B-TCR-2021-1112

SINUS + HEADACHE DAY

Drug Facts

ACTIVE INGREDIENT

Active ingredients (in each day caplet) | Purpose
Acetaminophen 325 mg | Pain reliever/fever reducer
Phenylephrine HCl 5 mg | Nasal decongestant

Uses

■ temporarily relieves these symptoms associated with hay fever or other upper respiratory allergies, and the common cold:
■ headache
■ sinus congestion and pressure
■ nasal congestion
■ minor aches and pains
■ helps decongest sinus openings and passages
■ promotes sinus drainage
■ helps clear nasal passages
■ temporarily reduces fever

SINUS + HEADACHE NIGHT

Drug Facts

ACTIVE INGREDIENT

Active ingredients (in each night caplet) | Purpose
Acetaminophen 325 mg | Pain reliever/fever reducer
Chlorpheniramine maleate 2 mg | Antihistamine
Phenylephrine HCl 5 mg | Nasal decongestant

Uses

■ temporarily relieves these symptoms associated with hay fever or other upper respiratory allergies, and the common cold:
■ headache
■ sinus congestion and pressure
■ nasal congestion
■ runny nose and sneezing
■ minor aches and pains
■ helps decongest sinus openings and passages
■ promotes sinus drainage
■ helps clear nasal passages
■ temporarily reduces fever

Warnings

Liver warning

Liver warning: This product contains acetaminophen. The maximum daily dose of this product is 10 caplets (3,250 mg acetaminophen) in 24 hours. Severe liver damage may occur if you take
■ more than 4,000 mg of acetaminophen in 24 hours
■ with other drugs containing acetaminophen
■ 3 or more alcoholic drinks every day while using this product

Allergy alert

Acetaminophen may cause severe skin reactions. Symptoms may include:
■ skin reddening
■ blisters
■ rash
If a skin reaction occurs, stop use and seek medical help right away.

Do not use

■ with any other drug containing acetaminophen (prescription or nonprescription). If you are not sure whether a drug contains acetaminophen, ask a doctor or pharmacist.
■ if you are now taking a prescription monoamine oxidase inhibitor (MAOI) (certain drugs for depression, psychiatric or emotional conditions, or Parkinson’s disease), or for 2 weeks after stopping the MAOI drug. If you do not know if your prescription drug contains an MAOI, ask a doctor or pharmacist before taking this product.
■ if you have ever had an allergic reaction to this product or any of its ingredients

Ask a doctor before use if you have

■ liver disease
■ heart disease
■ high blood pressure
■ thyroid disease
■ diabetes
■ trouble urinating due to an enlarged prostate gland
■ a breathing problem such as emphysema or chronic bronchitis
■ glaucoma

Ask a doctor or pharmacist before use if you are

■ taking the blood thinning drug warfarin
■ taking sedatives or tranquilizers

When using this product

■ do not exceed recommended dosage
In addition, when using Sinus + Headache Night:
■ excitability may occur, especially in children
■ drowsiness may occur
■ alcohol, sedatives, and tranquilizers may increase drowsiness
■ avoid alcoholic drinks
■ be careful when driving a motor vehicle or operating machinery

Stop use and ask a doctor if

■ nervousness, dizziness, or sleeplessness occur
■ pain or nasal congestion gets worse or lasts more than 7 days
■ fever gets worse or lasts more than 3 days
■ redness or swelling is present
■ new symptoms occur
These could be signs of a serious condition.

PREGNANCY OR BREAST FEEDING

If pregnant or breast-feeding, ask a health professional before use.

Overdose warning

In case of overdose, get medical help or contact a Poison Control Center right away (1-800-222-1222). Quick medical attention is critical for adults as well as for children even if you do not notice any signs or symptoms.

Directions

■ do not take more than directed (see overdose warning)

■ do not take Day and Night caplets at the same time
■ do not take more than a total of 10 caplets in 24 hours

adults and children 12 years and over | - take 2 caplets every 4 hours - swallow whole; do not crush, chew, or dissolve
children under 12 years | - ask a doctor

Other information

■ store between 20-25ºC (68-77ºF) in a dry place
■ retain carton for complete product information and warnings

Inactive ingredients

SINUS + HEADACHE DAY

acesulfame potassium, colloidal silicon dioxide, croscarmellose sodium, crospovidone, D&C yellow #10 aluminum lake, FD&C blue #1 aluminum lake, FD&C red #40 aluminum lake, flavor, magnesium stearate, microcrystalline cellulose, polyethylene glycol, polyvinyl alcohol, povidone, pregelatinized starch, propylene glycol, stearic acid, talc, titanium dioxide

SINUS + HEADACHE NIGHT

acesulfame potassium, colloidal silicon dioxide, corn starch, croscarmellose sodium, crospovidone, flavor, iron oxide yellow, magnesium stearate, microcrystalline cellulose, polyethylene glycol, polyvinyl alcohol, povidone, pregelatinized starch, propylene glycol, stearic acid, talc, titanium dioxide

PRINCIPAL DISPLAY PANEL

TopCare® health

NDC 36800-349-02

For Adults

Sinus + Headache Day + Night

DAYTIME

NON-DROWSY

PAIN RELIEVER/FEVER REDUCER - ACETAMINOPHEN

NASAL DECONGESTANT - PHENYLEPHRINE HCl

DAY CAPLET RELIEVES:

• Sinus Headache

• Sinus Pressure

• Nasal Congestion

actual size

12 COOL TASTE CAPLETS

NIGHTTIME

PAIN RELIEVER/FEVER REDUCER - ACETAMINOPHEN

NASAL DECONGESTANT - PHENYLEPHRINE HCl

ANTIHISTAMINE* - CHLORPHENIRAMINE MALEATE*

NIGHT CAPLET RELIEVES:

• Sinus Headache

• Sinus Pressure

• Nasal Congestion

• Runny Nose*

*Antihistamine in Nighttime Only

actual size

8 COOL TASTE CAPLETS